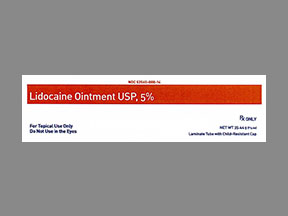 DRUG LABEL: lidocaine
NDC: 80175-0008 | Form: OINTMENT
Manufacturer: Central Packaging
Category: prescription | Type: HUMAN PRESCRIPTION DRUG LABEL
Date: 20210223

ACTIVE INGREDIENTS: LIDOCAINE 50 mg/1 g

INDICATIONS AND USAGE

Lidocaine Ointment USP, 5% is indicated for production of anesthesia of accessible mucous membranes of the oropharynx.It is also useful as an anesthetic lubricant for intubation and for the temporary relief of pain associated with minor burns, including sunburn, abrasions of the skin, and insect bites.

CONTRAINDICATIONS

Lidocaine is contraindicated in patients with a known history of hypersensitivity to local anesthetics of the amide type or to other components of Lidocaine Ointment USP, 5%.
Frame Style Transparent Dressing are contraindicated as a primary dressing on moderately to heavily draining wounds. Avoid repeated applications on patients with thin or fragile skin that may result in skin damage.